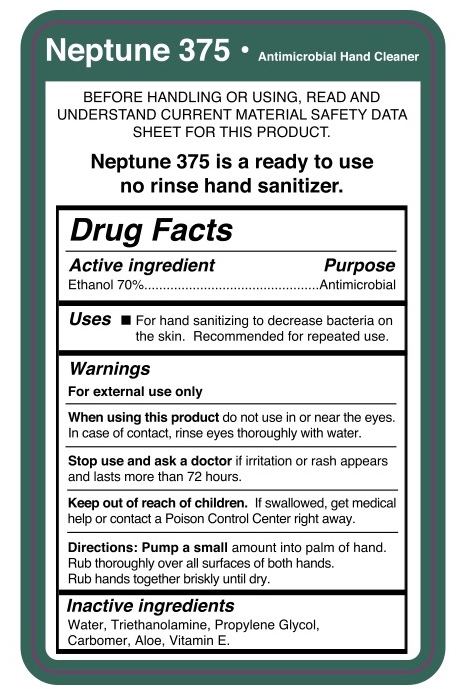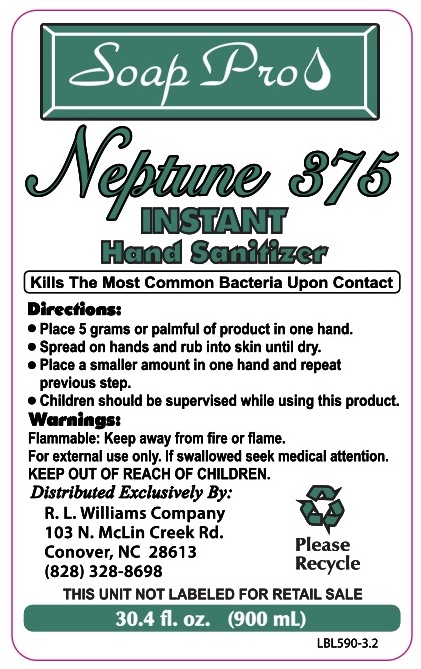 DRUG LABEL: Neptune 375 INSTANT Hand Sanitizer
NDC: 23590-130 | Form: LIQUID
Manufacturer: R.L. Williams Company
Category: otc | Type: HUMAN OTC DRUG LABEL
Date: 20210104

ACTIVE INGREDIENTS: ALCOHOL 70 mL/100 mL
INACTIVE INGREDIENTS: ALPHA-TOCOPHEROL; TROLAMINE; PROPYLENE GLYCOL; WATER; ALOE; CARBOMER HOMOPOLYMER, UNSPECIFIED TYPE

Neptune 375 INSTANT Hand Sanitizer

R.L. Williams Company

Neptune 375 INSTANT Hand Sanitizer

Drug Facts

Active Ingredient(s)

Alcohol 70%

Purpose

Antimicrobial

Use

For hand sanitizing to decrease bacteria on the skin. Recommended for repeted use.

Warnings

For external use only.

When using this product, do not use in or near the eyes. In case of contact, rinse thoroughly with water.

- Stop use and ask a doctor if irritation or rash appears and lasts more than 72 hours.

Keep out of reach of children. If swallowed, get medical help or contact a Poison Control Center right away.

Directions

Directions: Pump a small amount into palm of hand. Rub thoroughly over all surfaces of both hands. Rub hands together briskly until dry.

Inactive ingredients

Water, Triethanolamine, Propylene Glycol, Carbomer, Aloe, Vitamin E.